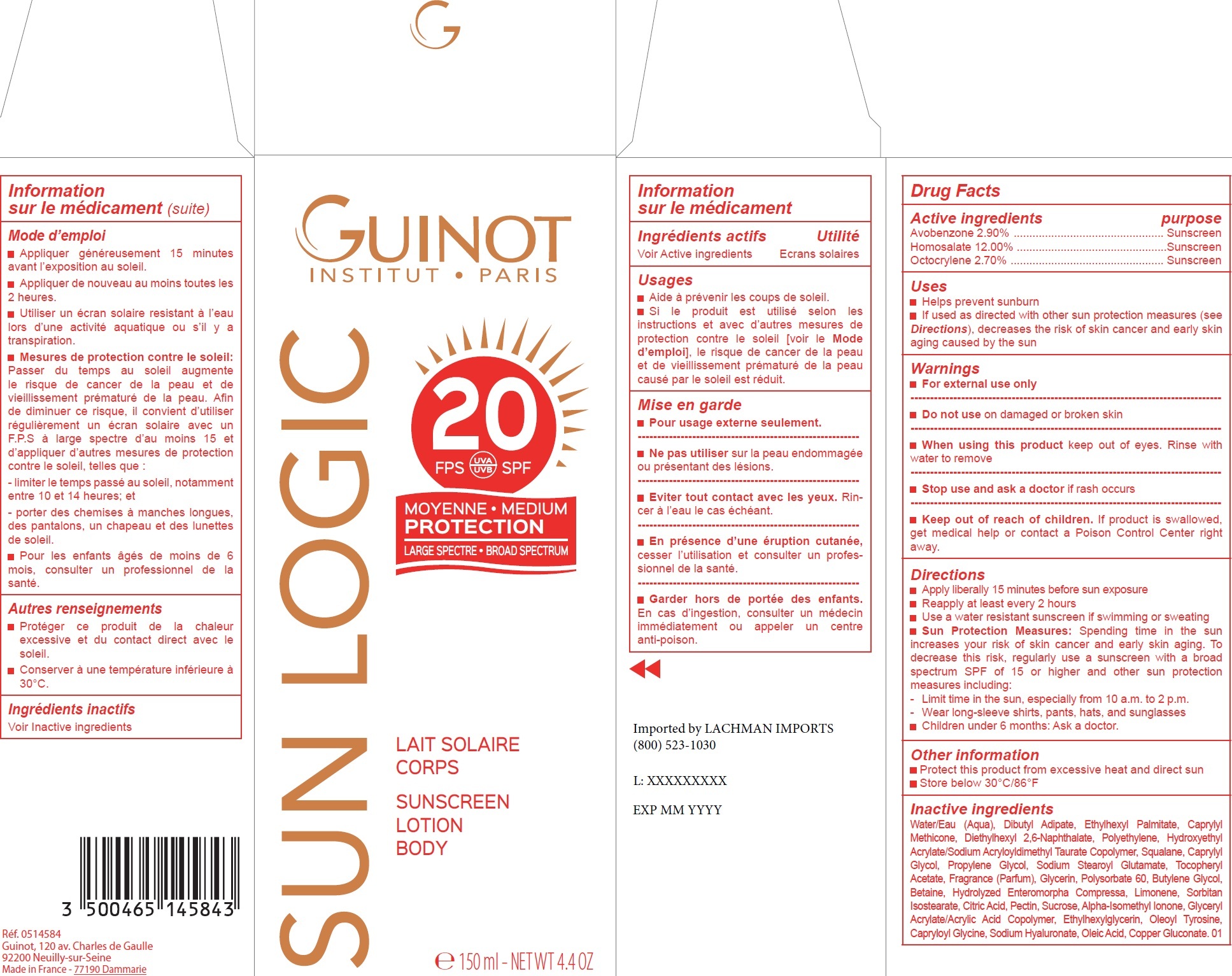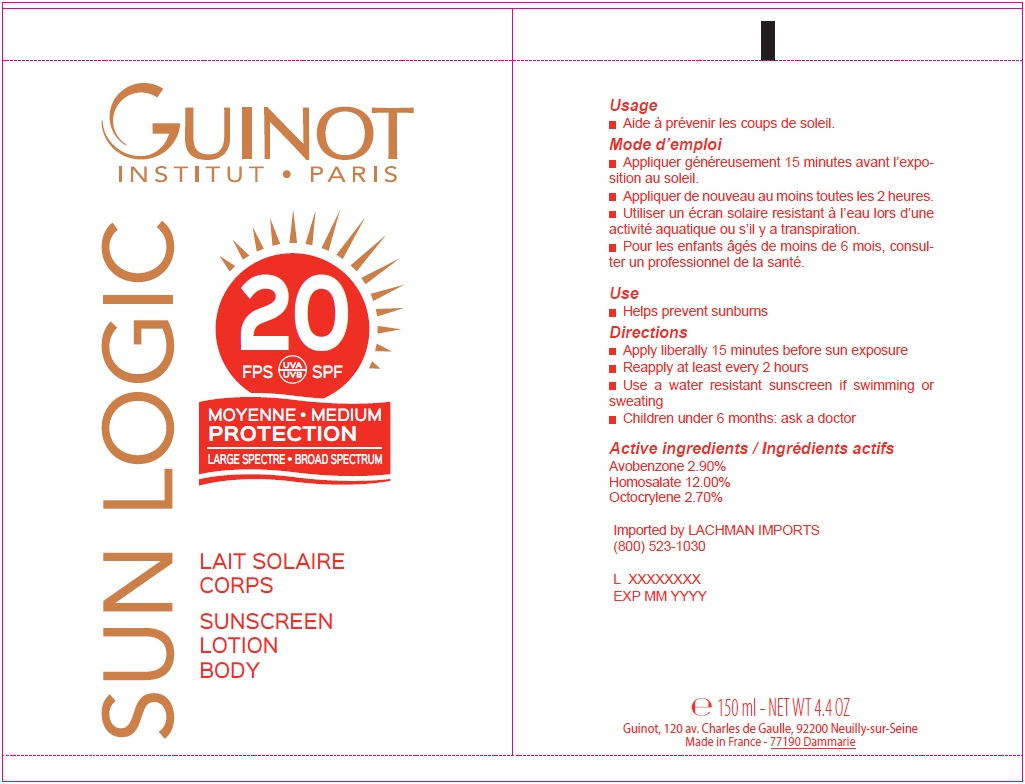 DRUG LABEL: Sun Logic Lait Solaire Corps SPF 20
NDC: 54181-010 | Form: LOTION
Manufacturer: Guinot
Category: otc | Type: HUMAN OTC DRUG LABEL
Date: 20251229

ACTIVE INGREDIENTS: AVOBENZONE 29 mg/1 mL; HOMOSALATE 120 mg/1 mL; OCTOCRYLENE 27 mg/1 mL
INACTIVE INGREDIENTS: WATER; DIBUTYL ADIPATE; ETHYLHEXYL PALMITATE; CAPRYLYL TRISILOXANE; DIETHYLHEXYL 2,6-NAPHTHALATE; HIGH DENSITY POLYETHYLENE; HYDROXYETHYL ACRYLATE/SODIUM ACRYLOYLDIMETHYL TAURATE COPOLYMER (100000 MPA.S AT 1.5%); SQUALANE; CAPRYLYL GLYCOL; PROPYLENE GLYCOL; SODIUM STEAROYL GLUTAMATE; .ALPHA.-TOCOPHEROL ACETATE; GLYCERIN; POLYSORBATE 60; BUTYLENE GLYCOL; BETAINE; HYDROLYZED ULVA COMPRESSA PROTEIN (ACID; 300-5000 MW); LIMONENE, (+)-; SORBITAN ISOSTEARATE; CITRIC ACID MONOHYDRATE; PECTIN; SUCROSE; ISOMETHYL-.ALPHA.-IONONE; ETHYLHEXYLGLYCERIN; OLEOYL TYROSINE; CAPRYLOYL GLYCINE; HYALURONATE SODIUM; OLEIC ACID

Sun Logic Lait Solaire Corps SPF 20

Active ingredients

Avobenzone 2.90%

Homosalate 12.00%

Octocrylene 2.70%

purpose

Sunscreen

Uses

- Helps prevent sunburn
- If used as directed with other sun protection measures (see Directions), decreases the risk of skin cancer and early skin aging caused by the sun

Warnings

- For external use only

Do not use

on damaged or broken skin

When using this product

keep out of eyes. Rinse with water to remove

Stop use and ask

a doctor if rash occurs

Keep out of reach of children.

If product is swallowed, get medical help or contact a Poison Control Center right away.

Directions

- Apply liberally 15 minutes before sun exposure
- Reapply at least every 2 hours
- Use a water resistant sunscreen if swimming or sweating
- Sun Protection Measures: Spending time in the sun increases your risk of skin cancer and early skin aging. To decrease this risk, regularly use a sunscreen with a broad spectrum SPF of 15 or higher and other sun protection measures including:

- Limit time in the sun, especially from 10 a.m. to 2 p.m.

- Wear long-sleeve shirts, pants, hats, and sunglasses

- Children under 6 months: Ask a doctor.

Other information

- Protect this product from excessive heat and direct sun
- Store below 30°C/86°F

Inactive ingredients

Water/Eau (Aqua), Dibutyl Adipate, Ethylhexyl Palmitate, Caprylyl Methicone, Diethylhexyl 2,6-Naphthalate, Polyethylene, Hydroxyethyl Acrylate/Sodium Acryloyldimethyl Taurate Copolymer, Squalane, Caprylyl Glycol, Propylene Glycol, Sodium Stearoyl Glutamate, Tocopheryl Acetate, Fragrance (Parfum), Glycerin, Polysorbate 60, Butylene Glycol, Betaine, Hydrolyzed Enteromorpha Compressa, Limonene, Sorbitan Isostearate, Citric Acid, Pectin, Sucrose, Alpha-Isomethyl Ionone, Glyceryl Acrylate/Acrylic Acid Copolymer, Ethylhexylglycerin, Oleoyl Tyrosine, Capryloyl Glycine, Sodium Hyaluronate, Oleic Acid, Copper Gluconate. 01